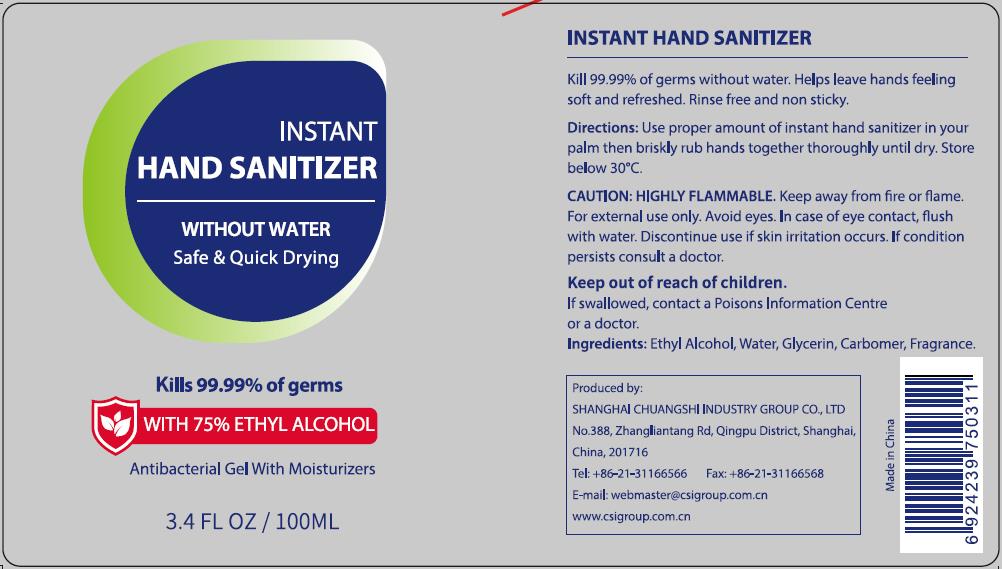 DRUG LABEL: INSTANT HAND SANITIZER
NDC: 73557-222 | Form: GEL
Manufacturer: Shanghai Chuangshi Industry Group Co., Ltd
Category: otc | Type: HUMAN OTC DRUG LABEL
Date: 20200409

ACTIVE INGREDIENTS: ALCOHOL 75 mL/100 mL
INACTIVE INGREDIENTS: GLYCERIN 0.5 mL/100 mL; WATER 23.85 mL/100 mL; CARBOMER HOMOPOLYMER, UNSPECIFIED TYPE 0.6 mL/100 mL; CLOVE 0.05 mL/100 mL

Instant Hand Sanitizer, 100mL

Active ingredient

Ethyl Alcohol

Inactive ingredient

Water
Carbomer
Glycerin
Fragrance

Purpose

Kill 99.9% germs without water.

Helps leave hands feeling soft and refreshed.

Rinse free and non sticky.

When using

Kill 99.9% germs without water.

Helps leave hands feeling soft and refreshed.

Do not use if beyonding directions.

Stop use

Discontinue use if skin irritaion occurs.

Ask doctor

Discontinue use if skin irritaion occurs. If condition persists consult a doctor.

Ask doctor/pharmacist

Discontinue use if skin irritaion occurs. If condition persists consult a doctor or pharmacist.

Keep out of reach of children

Questions

Please contact with us at the phone number +86-21-31166566 when you have any questions.

Pregnancy or breast feeding

Pregnant or breast feeding women shall follow doctor advice.

Indications & usage

Use proper amount of instant hand sanitizer in your palm then brisky rub hands together thoroughly until dry.

Store below 30oC.

Dosage & administration

Use it as needed, after following the usage instructions.

For external use only.

Dosage forms & strengths

This product is gel dosage form.
The active ingredient strength is 50%.

Warnings

HIGHLY FLAMMABLE. Keep away from fire or flame.

For external use only.

Avoid eyes. In case of eye contact, flush with water.

Discontinue use if skin irritaion occurs. If condition persists consult a doctor.